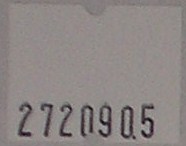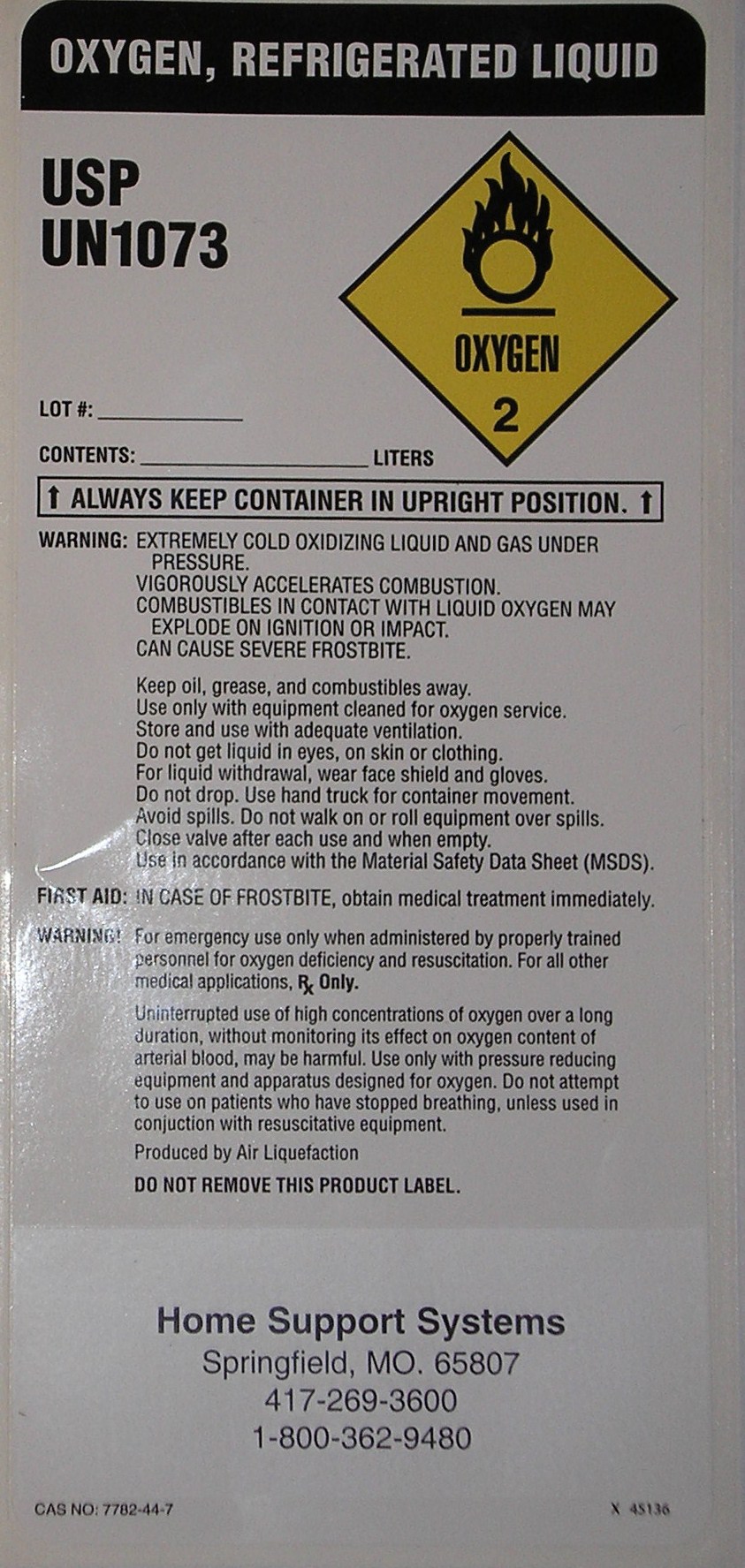 DRUG LABEL: Oxygen
NDC: 55221-0001 | Form: GAS
Manufacturer: Cox Health Home Support
Category: prescription | Type: HUMAN PRESCRIPTION DRUG LABEL
Date: 20091007

ACTIVE INGREDIENTS: Oxygen 99 L/100 L

Oxygen